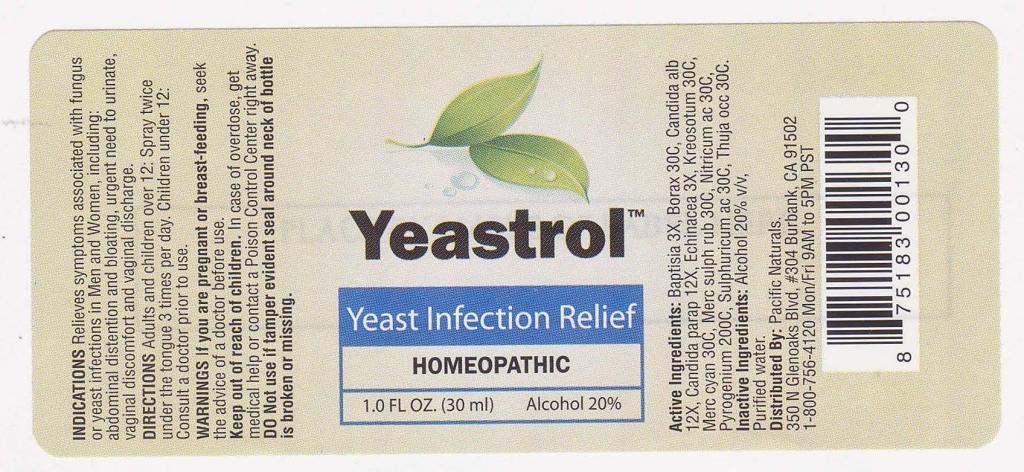 DRUG LABEL: Yeastrol
NDC: 50845-0023 | Form: SPRAY
Manufacturer: Liddell Laboratories, Inc.
Category: homeopathic | Type: HUMAN OTC DRUG LABEL
Date: 20110512

ACTIVE INGREDIENTS: BAPTISIA TINCTORIA ROOT 3 [hp_X]/1 mL; SODIUM BORATE 30 [hp_C]/1 mL; CANDIDA ALBICANS 12 [hp_X]/1 mL; CANDIDA PARAPSILOSIS 12 [hp_X]/1 mL; ECHINACEA 3 [hp_X]/1 mL; MERCURIC CYANIDE 30 [hp_C]/1 mL; MERCURIC SULFIDE 30 [hp_C]/1 mL; NITRIC ACID 30 [hp_C]/1 mL; RANCID BEEF 200 [hp_C]/1 mL; SULFURIC ACID 30 [hp_C]/1 mL; THUJA OCCIDENTALIS LEAFY TWIG 30 [hp_C]/1 mL; WOOD CREOSOTE 30 [hp_C]/1 mL
INACTIVE INGREDIENTS: WATER; ALCOHOL

Yeastrol

ACTIVE INGREDIENT

ACTIVE INGREDIENTS: Baptisia tinctoria 3X, Borax 30C, Candida albicans 12X, Candida parapsilosis 12X, Echinacea 3X, Kreosotum 30C, Mercurius cyanatus 30C, Mercurius sulphuratus ruber 30C, Nitricum acidum 30C, Pyrogenium 200C, Sulphuricum acidum 30C, Thuja occidentalis 30C.

PURPOSE

INDICATIONS: Relieves symptoms associated with fungus or yeast infections in Men and Women, including: abdominal distention and bloating, urgent need to urinate, vaginal discomfort and vaginal discharge.

WARNINGS

WARNINGS: If you are pregnant or breast-feeding, seek the advice of a doctor before use.

Keep out of reach of children. In case of overdose, get medical help or contact a Poison Control Center right away.

DO Not use if tamper evident seal around entire bottle is missing or broken.

DOSAGE AND ADMINISTRATION

DIRECTIONS: Adults and children over 12: Spray twice under the tongue 3 times per day. Children under 12: Consult a doctor prior to use.

INACTIVE INGREDIENT

INACTIVE INGREDIENTS: Organic alcohol 20% v/v, Purified water.

KEEP OUT OF REACH OF CHILDREN: In case of overdose, get medical help or contact a Poison Control Center right away.

INDICATIONS AND USAGE

INDICATIONS: Relieves symptoms associated with fungus or yeast infections in Men and Women, including: abdominal distention and bloating, urgent need to urinate, vaginal discomfort and vaginal discharge.

QUESTIONS

Distributed by:

Pacific Naturals

350 N. Glenoaks Blvd. #304,

Burbank, CA 91502

1-800-756-4120 Mon/Fri 9AM to 5PM PST

PACKAGE LABEL

Yeastrol

Yeast Infection Relief

HOMEOPATHIC

1.0 FL OZ (30 ml)